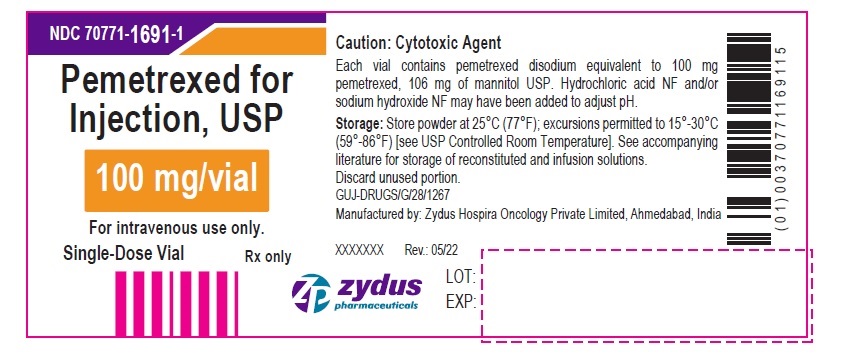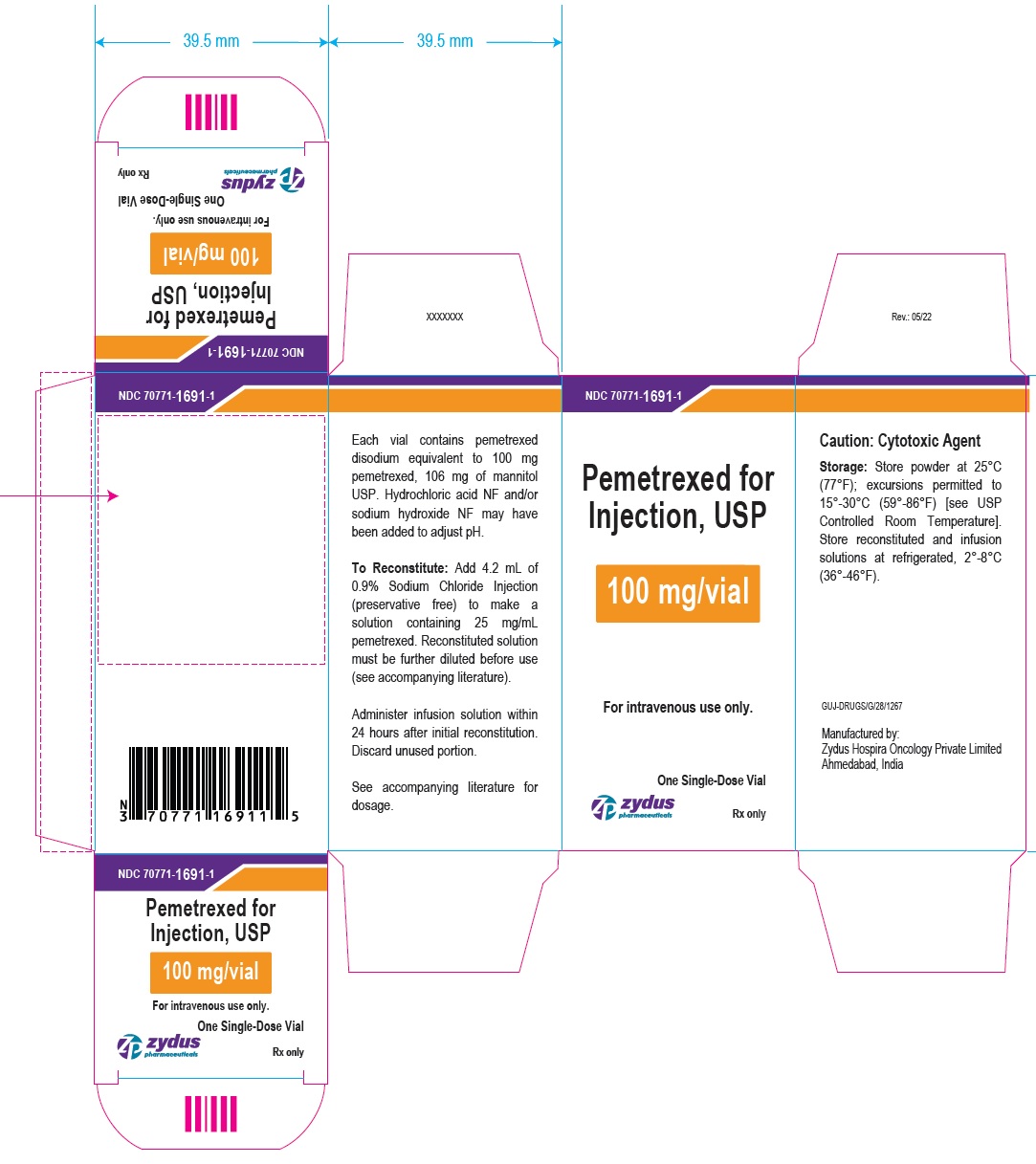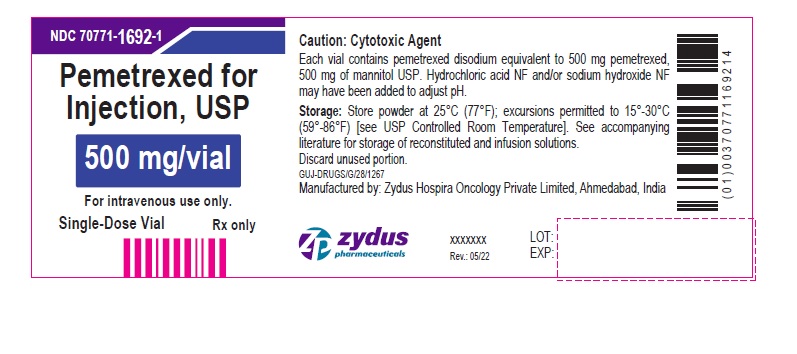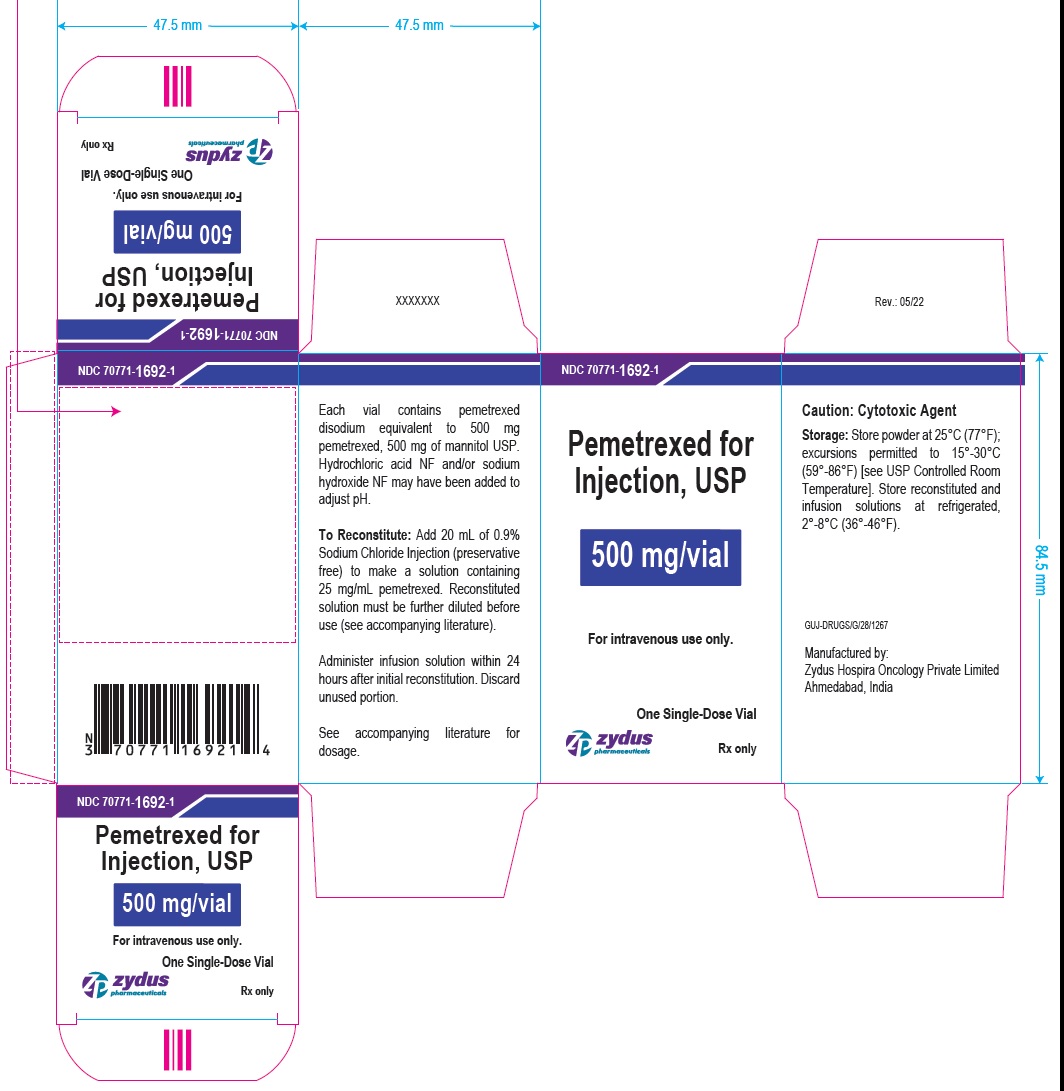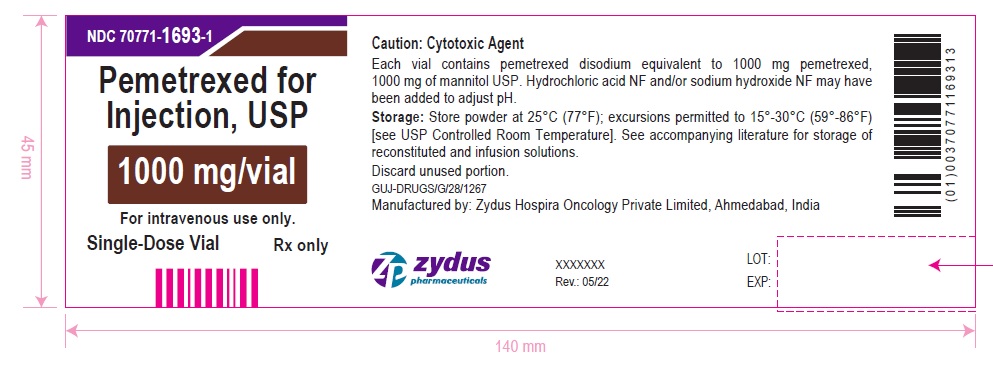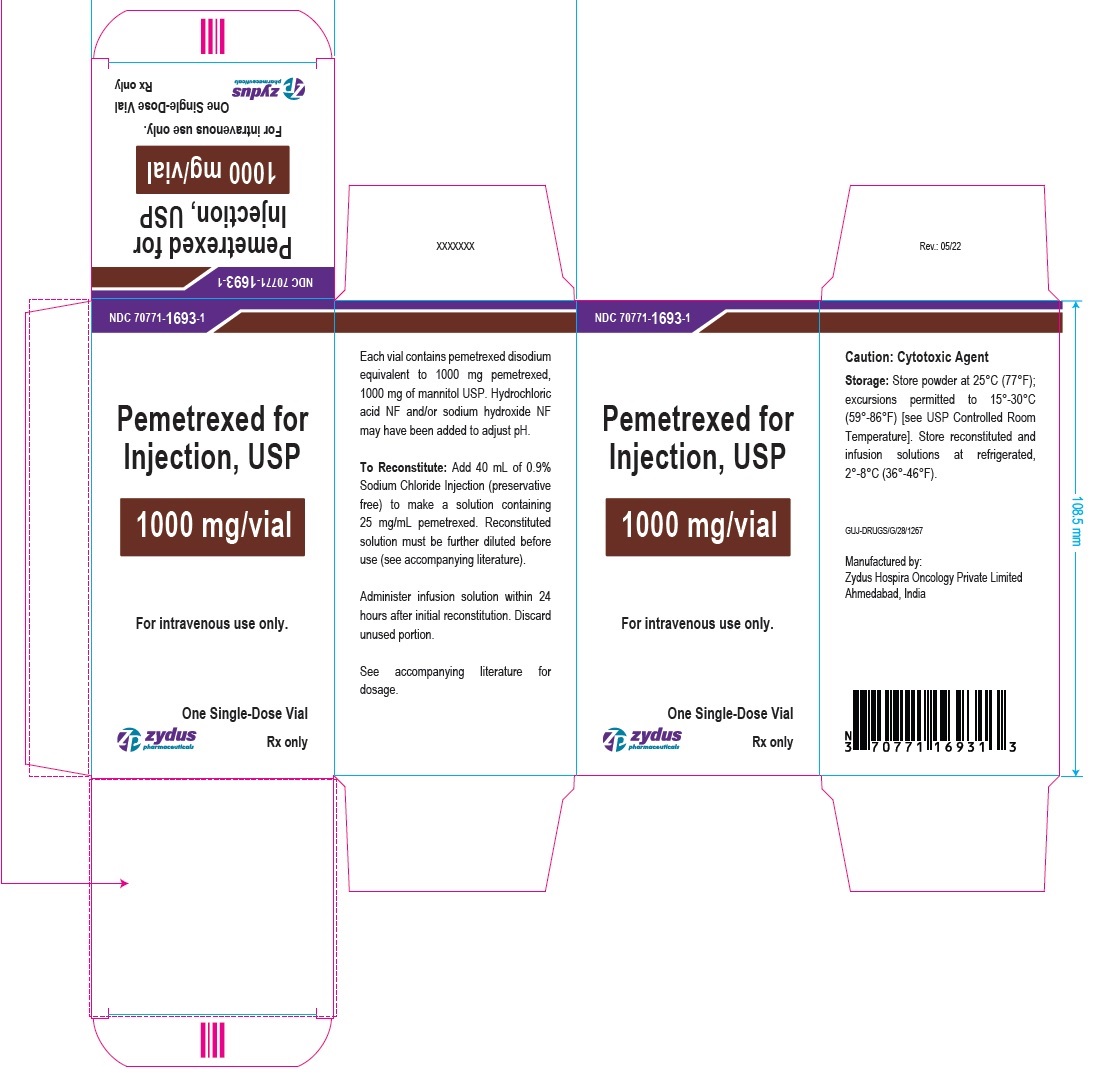 DRUG LABEL: pemetrexed
NDC: 70771-1691 | Form: INJECTION, POWDER, LYOPHILIZED, FOR SOLUTION
Manufacturer: Zydus Lifesciences Limited
Category: prescription | Type: HUMAN PRESCRIPTION DRUG LABEL
Date: 20220526

ACTIVE INGREDIENTS: PEMETREXED DISODIUM 100 mg/4 mL
INACTIVE INGREDIENTS: MANNITOL 106 mg/4 mL; HYDROCHLORIC ACID; SODIUM HYDROXIDE

Pemetrexed for injection, for Intravenous Use

PACKAGE LABEL.PRINCIPAL DISPLAY PANEL

NDC 70771-1691-1

Pemetrexed for Injection, USP

100 mg/vial

For intravenous use only.

Single-Dose Vial

Rx only

NDC 70771-1691-1

Pemetrexed for Injection, USP

100 mg/vial

For intravenous use only.

One Single-Dose Vial Carton

Rx only

NDC 70771-1692-1

Pemetrexed for Injection, USP

500 mg/vial

For intravenous use only.

Single-Dose Vial

Rx only

NDC 70771-1692-1

Pemetrexed for Injection, USP

500 mg/vial

For intravenous use only.

One Single-Dose Vial Carton

Rx only

NDC 70771-1693-1

Pemetrexed for Injection, USP

1000 mg/vial

For intravenous use only.

Single-Dose Vial

Rx only

NDC 70771-1693-1

Pemetrexed for Injection, USP

1000 mg/vial

For intravenous use only.

One Single-Dose Vial Carton

Rx only